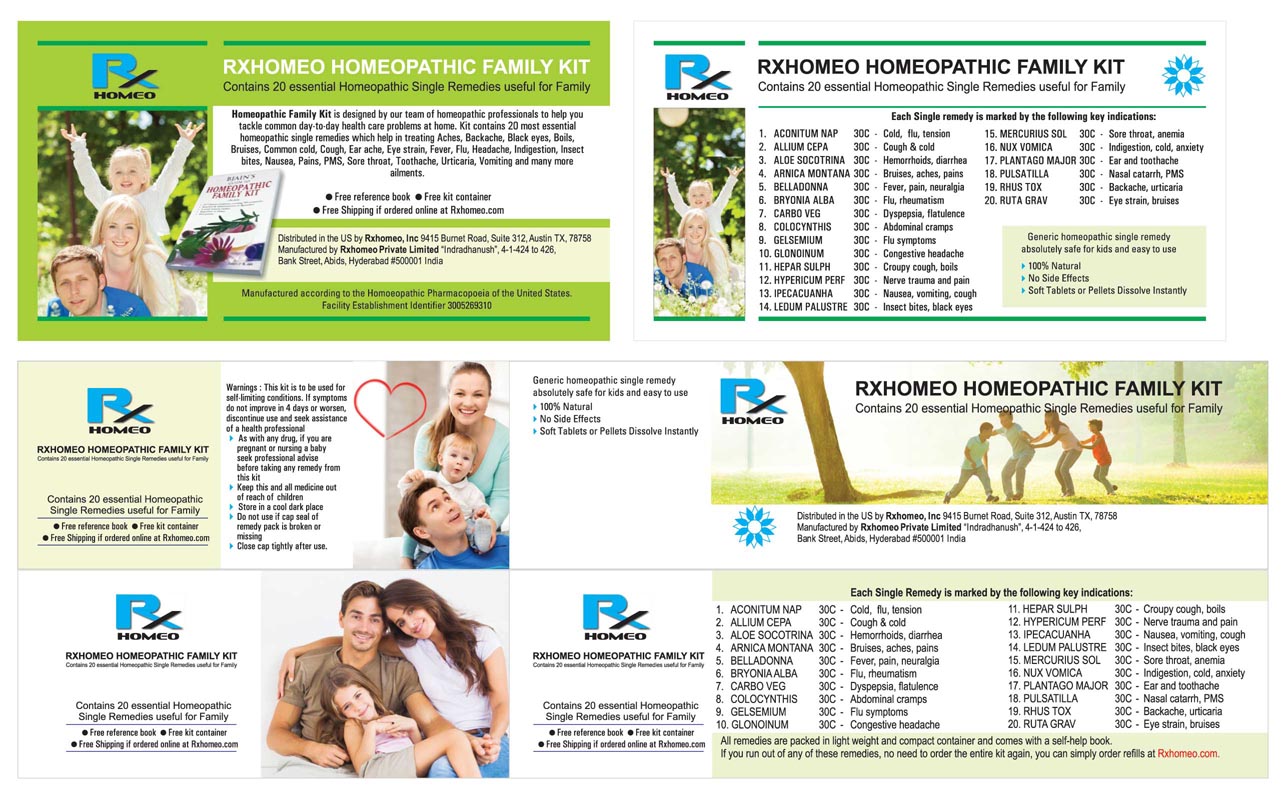 DRUG LABEL: Rxhomeo Homeopathic Family Kit
NDC: 15631-2451 | Form: KIT | Route: ORAL
Manufacturer: Rxhomeo Private Limited d.b.a.
Category: homeopathic | Type: HUMAN OTC DRUG LABEL
Date: 20160607

ACTIVE INGREDIENTS: ACONITUM NAPELLUS 3 [hp_X]/1 1; ONION 1 [hp_X]/1 1; ALOE 1 [hp_X]/1 1; ARNICA MONTANA 3 [hp_X]/1 1; ATROPA BELLADONNA 3 [hp_X]/1 1; BRYONIA ALBA ROOT 3 [hp_X]/1 1; ACTIVATED CHARCOAL 1 [hp_X]/1 1; CITRULLUS COLOCYNTHIS FRUIT PULP 3 [hp_X]/1 1; EUPHRASIA STRICTA 1 [hp_X]/1 1; GELSEMIUM SEMPERVIRENS ROOT 3 [hp_X]/1 1; NITROGLYCERIN 6 [hp_X]/1 1; CALCIUM SULFIDE 1 [hp_X]/1 1; HYPERICUM PERFORATUM 3 [hp_X]/1 1; IPECAC 3 [hp_X]/1 1; MERCURIUS SOLUBILIS 6 [hp_X]/1 1; STRYCHNOS NUX-VOMICA SEED 3 [hp_X]/1 1; PLANTAGO MAJOR 1 [hp_X]/1 1; PULSATILLA VULGARIS 1 [hp_X]/1 1; TOXICODENDRON PUBESCENS LEAF 3 [hp_X]/1 1; CALENDULA OFFICINALIS FLOWERING TOP 1 [hp_X]/1 g
INACTIVE INGREDIENTS: SUCROSE; SUCROSE; SUCROSE; SUCROSE; SUCROSE; SUCROSE; SUCROSE; SUCROSE; SUCROSE; SUCROSE; SUCROSE; SUCROSE; SUCROSE; SUCROSE; SUCROSE; SUCROSE; SUCROSE; SUCROSE; SUCROSE; ALOE

ACTIVE INGREDIENT

ACONITUM NAPELLUS

ALLIUM CEPA

ALOE SOCOTRINA

ARNICA MONTANA

BELLADONNA

BRYONIA ALBA

CALENDULA OFFICINALIS

CARBO VEGETABILIS

COLOCYNTHIS

EUPHRASIA OFFICINALIS

GELSEMIUM SEMPERVIRENS

GLONOINUM

HEPAR SULPHURIS CALCAREUM

HYPERICUM PERFORATUM

IPECACUANHA

MERCURIUS SOLUBILIS

NUX VOMICA

PLANTAGO MAJOR

PULSATILLA

RHUS TOXICODENDRON

CALENDULA OFF GEL

USES

ACONITUM NAPELLUS | 3X | Cold, Flu, Tension
ALLIUM CEPA | 1X | Cough & Cold
ALOE SOCOTRINA | 1X | Hemorrhoids, Diarrhea
ARNICA MONTANA | 3X | Bruises, Aches, Pains
BELLADONNA | 3X | Fever, Pain, Neuralgia
BRYONIA ALBA | 3X | Flu, Rheumatism
CARBO VEGETABILIS | 1X | Dyspepsia, Flatulence
COLOCYNTHIS | 3X | Abdominal Cramps
EUPHRASIA OFFICINALIS | 1X | Conjunctivitis
GELSEMIUM SEMPERVIRENS | 3X | Flu Symptoms
GLONOINUM | 6X | Congestive Headache
HEPAR SULPHURIS CALCAREUM | 1X | Croupy Cough, Boils
HYPERICUM PERFORATUM | 3X | Nerve Trauma & Pain
IPECACUANHA | 3X | Nausea, Vomiting, Cough
MERCURIUS SOLUBILIS | 6X | Sore Throat, Anemia
NUX VOMICA | 3X | Indigestion, Cold, Anxiety
PLANTAGO MAJOR | 1X | Ear & Toothache
PULSATILLA | 1X | Nasal Catarrh, Pms
RHUS TOXICODENDRON | 3X | Backache, Urticaria
CALENDULA OFF GEL | Tinc | Minor cuts, scrapes, burns, skin irritation and diaper rash

INDICATIONS

Condition listed above or as directed by the physician

DOSAGE

PELLETS included in the Kit

Adults- Take 4 or 6 Pellets by mouth, three times daily or as suggested by physician. Children 2 years and older- take 1/2 the adult dose.

GEL OINTMENT included in the Kit

Apply a thin layer of Gel to the affected area, repeat 3 times a day or as needed.

WARNINGS

This product is to be used for self-limiting conditions

STOP USE

If symptoms do not improve in 4 days, or worsen, discontinue use and seek assistance of health professional

KEEP OUT OF REACH OF CHILDREN

Keep this and all medication out of reach of children

Do not use if capseal is broken or missing.
Close the cap tightly after use.

INACTIVE INGREDIENTS

Sucrose for Pellets.

Aloe Vera Gel for Ointment

STORAGE

Store in a cool dark place

QUESTIONS OR COMMENTS

www.Rxhomeo.com | 1.888.2796642 | info@rxhomeo.com
Rxhomeo, Inc 9415 Burnet Road, Suite 312, Austin, TX 78758